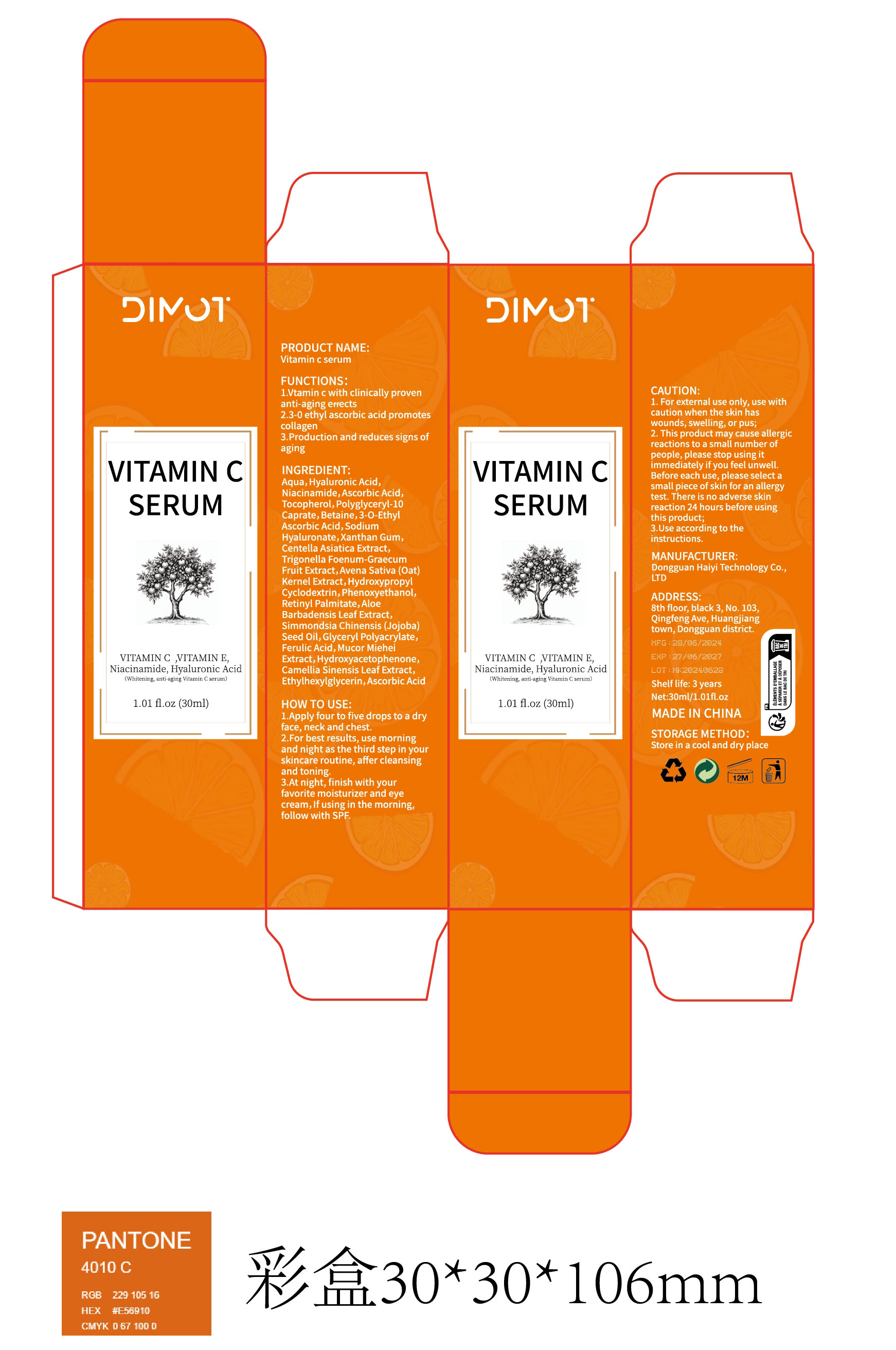 DRUG LABEL: Vitamin c serum
NDC: 84732-039 | Form: LIQUID
Manufacturer: Dongguan Haiyi Technology Co.,Ltd.
Category: otc | Type: HUMAN OTC DRUG LABEL
Date: 20241011

ACTIVE INGREDIENTS: ASCORBIC ACID 1 mg/100 mL
INACTIVE INGREDIENTS: NIACINAMIDE; CENTELLA ASIATICA TRITERPENOIDS; BETAINE; TOCOPHEROL; 3-O-ETHYL ASCORBIC ACID; FENUGREEK SEED; POLYGLYCERYL-10 CAPRATE; WATER; PEG-9 DIGLYCIDYL ETHER/SODIUM HYALURONATE CROSSPOLYMER; HYALURONIC ACID; OAT

Active ingredient

Ascorbic Acid

Inactive ingredient

Aqua,Hyaluronic Acid,Niacinamide,Ascorbic Acid.Tocopherol,Polyglyceryl-10Caprate,Betaine,3-0-EthylAscorbic Acid,sodiumHyaluronate,Xanthan Gum,Centella Asiatica Extract,Trigonella Foenum-GraecumFruit Extract,Avena Sativa (Oat)Kernel Extract,HydroxypropylCyclodextrin,Phenoxyethanol,Retinyl Palmitate,AloeBarbadensis Leaf Extract,Simmondsia Chinensis (Jojoba)Seed oil,Glyceryl Polyacrylate,Ferulic Acid,Mucor MieheiExtract,Hydroxyacetophenone.Camellia Sinensis Leaf Extract,Ethylhexylglycerin,Ascorbic Acid

Purpose section

1.Vtamin c with clinically provenanti-aging erects

2.3-0 ethyl ascorbic acid promotescollagen

3 Production and reduces signs ofaging

WARING

1. For external use only, use withcaution when the skin haswounds,swelling, or pus;

2. This product may cause allergicreactions to a small number ofpeople, please stop using itimmediately if you feel unwell.Before each use, please select asmall piece of skin for an allergytest. There is no adverse skinreaction 24 hours before usingthis product;

3.Use according to theinstructions.

stop use

This product may cause allergic reactions in asmall number of people

1f youexperience any discomfort,please stop using it immediately.

not use

Not suitable for use by children, pregnantor breast feeding people.

OUT OF CHILDREN

KEEP THE PRODUCT OUT OF REACH OF CHILDREN to

HOW TO USE

1.Apply four to five drops to a dry face, neck and chest.
2. For best results, use morning and night as the third step in your skincare routine, affer cleansing and toning

3 .At night, finish with yourfavorite moisturizer and eyecream.lf using in the morning,follow with SPF.

Dosage

take an appropriateamount,Use 2-3 times a week